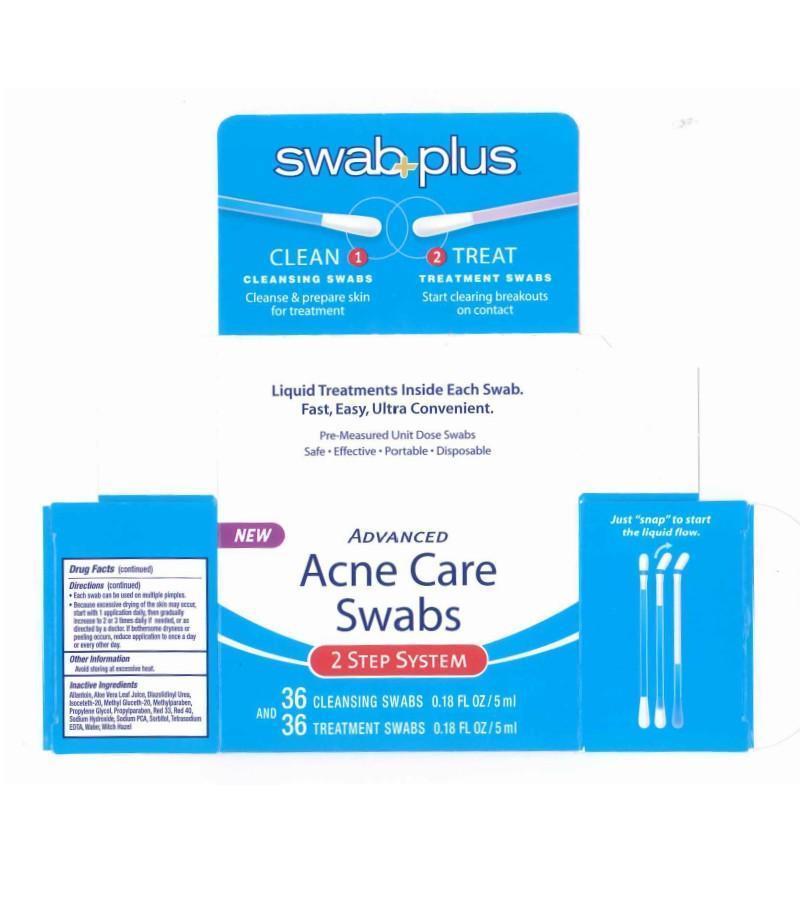 DRUG LABEL: Advance Acne Care
NDC: 65734-740 | Form: KIT | Route: TOPICAL
Manufacturer: Swabplus Inc.
Category: otc | Type: HUMAN OTC DRUG LABEL
Date: 20150323

ACTIVE INGREDIENTS: SILVER 0.1 mg/10 mL; SALICYLIC ACID 20 mg/1 mL
INACTIVE INGREDIENTS: SODIUM LAURYL SULFATE; CITRIC ACID ACETATE; WATER; ALLANTOIN; ALOE VERA LEAF; DIAZOLIDINYL UREA; ISOCETETH-20; METHYL GLUCETH-20; METHYLPARABEN; PROPYLENE GLYCOL; PROPYLPARABEN; SODIUM HYDROXIDE; SODIUM; SORBITAN; WATER; WITCH HAZEL

Advance Acne Care Swab

Drug Facts Active Ingredients

Advance Acne Care Swabs step 1

Silver 0.001%

Advance Acne Care Swabs Step 2

Salicylic Acid 2.0%

Purpose

For skin acne medication

Uses

When using this product. Avoid contact with eyes. If contact occures. flush throughly with water. Using other topical acne medications at teh same time or immediately following use this product may increase dryness or irrtation of the skin. If this occures, only one medication shoukld be used unless directed by a doctor. Do not insert in teh canal.

Keep out of reach of children

If swallowed, get medical help or contact a Poison Control Center right away.

Directions

- Do not use if label seal is broken prior to purchase.Keep swabs in original container when not in use. Treatment Swabs have a red color band.
- Use Cleansinh swab to cleanse the skin throughly before applying medication.
- Hold the swab vertically, with the color ring band tip upwards.
- Bend the tip at the color band to one side until it snaps. Medicine will flow to theother end.
- Cover the entire affected area with a thin layer 1 to 3 times daily. Discard swab after use.
- Each swab can be used on multipe pimples.
- Because excesssive drying of the skin may occur start with1 application daiky then gradually increase to 2 or 3 times daily if needed, or as direcvted by a doctor. If bothersome dryness or peeling occurs, reduce application to once a day or every othr day.

Warnings

For external use only.

Other information

Avoid storing at excessive heat.

Inactive Ingredients

Allantoin, Aloe Vera leaf Juice, Diazolidinyl Urea, Isoceteth-20, Methyl Gluceth-20, Methylparaben, Propylene Glycol, Propylparaben, Red 33, Red 40, Sodium Hydroxide, Sodium PCA, Sorbitol, Tetrasodium EDTA, Water, Witch Hazel.

Water, Sodium Lauryl Sulfate, Citric Acid, Silver.

Package carton

Image of Acne Care Carton